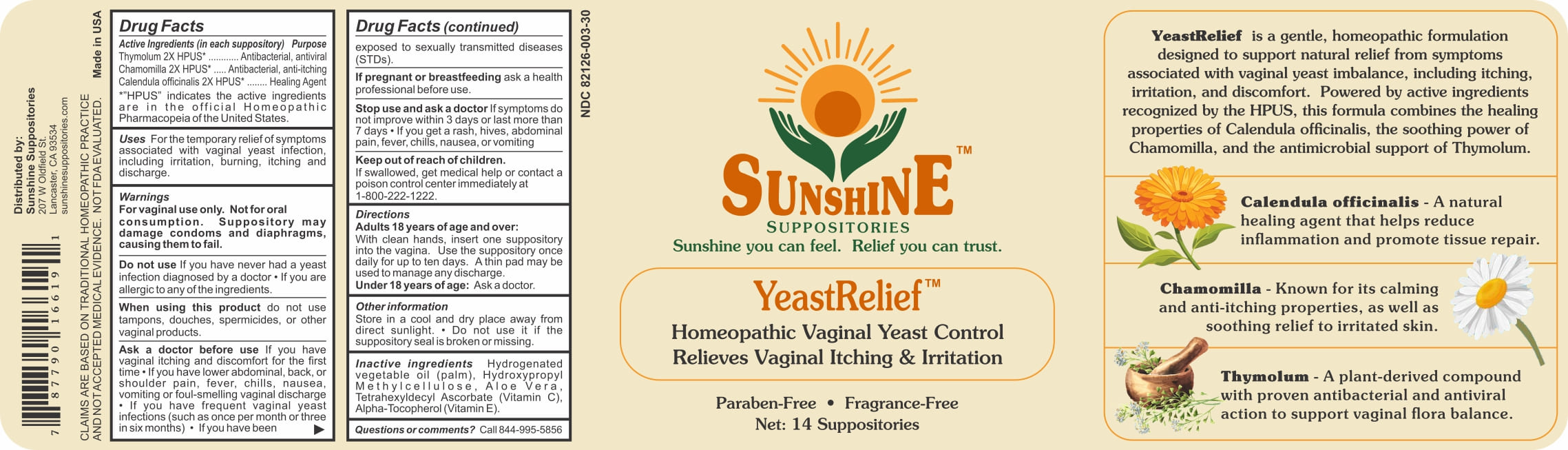 DRUG LABEL: Sunshine YeastRelief
NDC: 82126-003 | Form: SUPPOSITORY
Manufacturer: Apcco Labs, Inc
Category: homeopathic | Type: HUMAN OTC DRUG LABEL
Date: 20250618

ACTIVE INGREDIENTS: MATRICARIA CHAMOMILLA WHOLE 2 [hp_X]/1 mg; THYMOL 2 [hp_X]/1 mg; CALENDULA OFFICINALIS FLOWER 2 [hp_X]/1 mg
INACTIVE INGREDIENTS: HYPROMELLOSE 2910 (15 MPA.S); HYDROGENATED PALM OIL; ALOE VERA LEAF; ASCORBYL TETRAISOPALMITATE; .ALPHA.-TOCOPHEROL ACETATE, DL-

Apcco Labs, YeastRelief

ACTIVE INGREDIENTS:

Thymolum 2X HPUS*.......Antibacterial, antiviral

Chamomilla 2X HPUS*.... Antibacterial, anti-itching

Calendula officinalis 2X HPUS*........Healing Agent

*"HPUS" indicates the active ingredients are in the official Homeopathic

Pharmacopeia of the United States.

PURPOSE:

Antibacterial, antiviral

Antibacterial, anti-itching

Healing Agent

INDICATIONS:

For the temporary relief of symptoms associated with vaginal yeast infection, including irritation, burning,

itching and discharge.

WARNINGS:

For vaginal use only. Not for oral consumption. Suppository may damage condoms and diaphragms, causing them to fail.

Do not use If you have never had a yeast infection diagnosed by a doctor • If you are allergic to any of the ingredients.

When using this product, do not use tampons, douches, spermicides, or other vaginal products.

Ask a doctor before use If you have vaginal itching and discomfort for the first time • If you have lower abdominal, back, or shoulder pain,

fever,

chills,

nausea,

vomiting or foul-smelling vaginal discharge

• If you have frequent vaginal

yeast

infections (such as once per month or three in six months) • If you have been exposed to sexually transmitted diseases (STDs).

Stop use and ask a doctor If symptoms do not improve within 3 days or last more than 7 days • If you get a rash, hives, abdominal pain, fever, chills, nausea, or vomiting

If pregnant or breast feeding, ask a health professional before use.

KEEP OUT OF REACH OF CHILDREN:

If swallowed, get medical help or contact a poison control center immediately at 1-800-222-1222.

DIRECTIONS:

Adults 18 years of age and over:

With clean hands, insert one suppository into the vagina. Use the suppository once daily for up to ten days. A thin pad may be used to manage any discharge.

Under 18 years of age: Ask a doctor.

INACTIVE INGREDIENTS:

Hydrogenated

Hydroxypropyl

Methylcellulose,

Aloe

Vera

Tetrahexyldecyl Ascorbate (Vitamin C),

Alpha-Tocopherol (Vitamin E).

OTHER INFORMATION:

Store in a cool and dry place away from direct sunlight.

• Do not use if the suppository seal is broken or missing.

QUESTIONS:

Call 844-995-5856